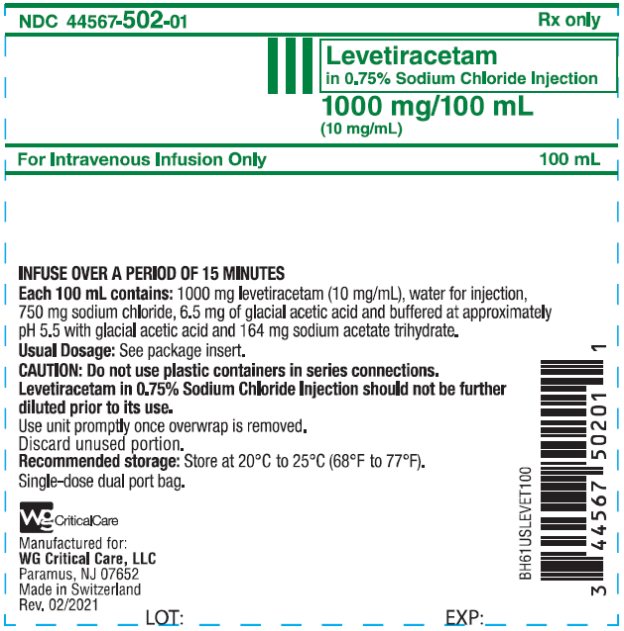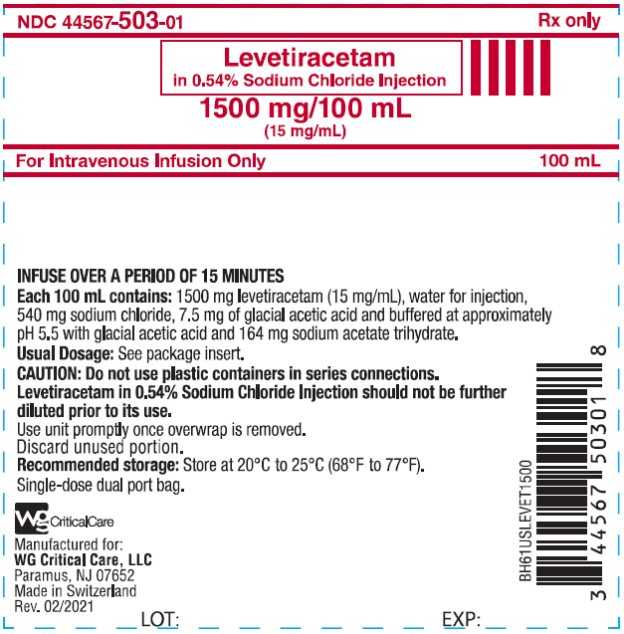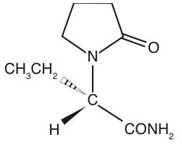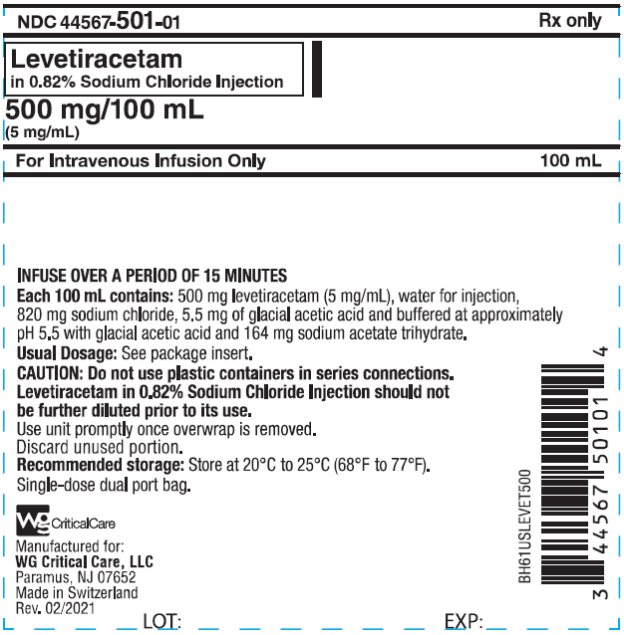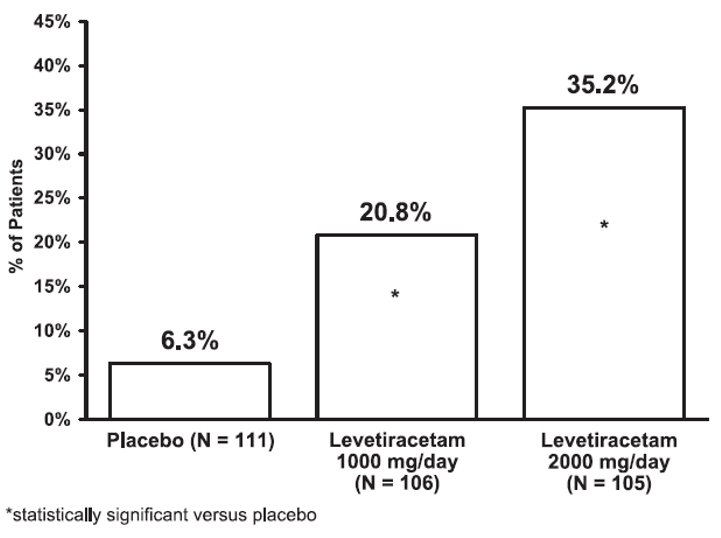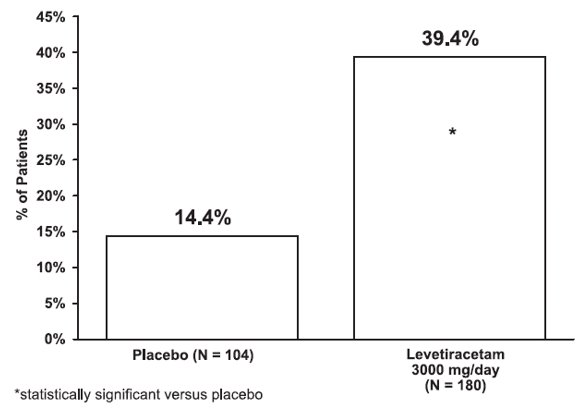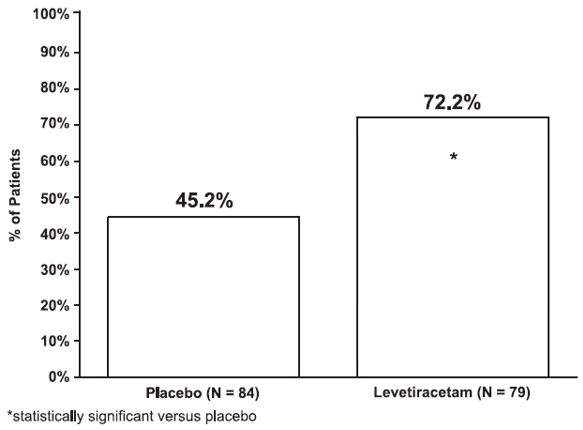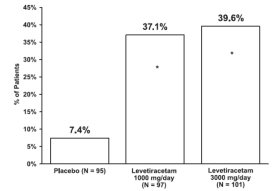 DRUG LABEL: Levetiracetam
NDC: 44567-501 | Form: INJECTION
Manufacturer: WG Critical Care, LLC
Category: prescription | Type: HUMAN PRESCRIPTION DRUG LABEL
Date: 20240329

ACTIVE INGREDIENTS: LEVETIRACETAM 5 mg/1 mL
INACTIVE INGREDIENTS: WATER; SODIUM CHLORIDE; ACETIC ACID; SODIUM ACETATE

HIGHLIGHTS OF PRESCRIBING INFORMATION

These highlights do not include all the information needed to use LEVETIRACETAM IN SODIUM CHLORIDE INJECTION safely and effectively. See full prescribing information for LEVETIRACETAM IN SODIUM CHLORIDE INJECTION.
LEVETIRACETAM IN SODIUM CHLORIDE injection, for intravenous use
Initial U.S. Approval: 1999

RECENT MAJOR CHANGES

Warnings and Precautions (5.5) 3/2024

1 INDICATIONS AND USAGE

Levetiracetam in Sodium Chloride Injection is indicated for adjunct therapy in adults (≥16 years of age) with the following seizure types when oral administration is temporarily not feasible:

- Partial-onset seizures (1.1)
- Myoclonic seizures in patients with juvenile myoclonic epilepsy (1.2)
- Primary generalized tonic-clonic seizures (1.3)

2 DOSAGE AND ADMINISTRATION

- For intravenous infusion only (2.1)
- Do not dilute prior to its use (2.1)
- Administer dose-specific bag intravenously over 15-minutes (2.1)

Initial Exposure to Levetiracetam

- Partial-Onset Seizures: Initial dose is 500 mg twice daily. Increase by 500 mg twice daily every 2 weeks to a maximum recommended dose of 1500 mg twice daily (2.2).
- Myoclonic Seizures in Patients with Juvenile Myoclonic Epilepsy: Initial dose is 500 mg twice daily. Increase by 500 mg twice daily every 2 weeks to the recommended dose of 1500 mg twice daily. (2.2).
- Primary Generalized Tonic-Clonic Seizures: Initial dose is 500 mg twice daily. Increase by 500 mg twice daily every 2 weeks to the recommended dose of 1500 mg twice daily. (2.2).

Switching from or to oral Levetiracetam: The total daily dosage/frequency of levetiracetam injection should be equivalent to those of oral levetiracetam (2.3, 2.4).

Renal Impairment: Dose adjustment necessary based on creatinine clearance (2.5).

3 DOSAGE FORMS AND STRENGTHS

Levetiracetam in Sodium Chloride Injection in single-dose bags:

- Levetiracetam in 0.82% sodium chloride (500 mg/100 mL) (5 mg/mL) (3)
- Levetiracetam in 0.75% sodium chloride (1000 mg/100 mL) (10 mg/mL) (3)
- Levetiracetam in 0.54% sodium chloride (1500 mg/100 mL) (15 mg/mL) (3)

4 CONTRAINDICATIONS

- Known hypersensitivity to levetiracetam; angioedema and anaphylaxis have occurred (4)

5 WARNINGS AND PRECAUTIONS

- Psychiatric Reactions: Behavioral abnormalities including psychotic symptoms, suicidal ideation, irritability, and aggressive behavior have been observed. Monitor patients for psychiatric signs and symptoms (5.1)
- Somnolence and Fatigue: Monitor patients for these symptoms and advise patients not to drive or operate machinery until they have gained sufficient experience on levetiracetam (5.2)
- Serious Dermatological Reactions: Discontinue Levetiracetam at the first sign of rash unless clearly not drug related. (5.4)
- Drug Reaction with Eosinophilia and Systemic Symptoms (DRESS)/Multiorgan Hypersensitivity: Discontinue if no alternative etiology (5.5)
- Coordination Difficulties: Monitor for ataxia, abnormal gait, and incoordination. (5.6)
- Withdrawal Seizures: Levetiracetam must be gradually withdrawn (5.7)

6 ADVERSE REACTIONS

- Most common adverse reactions (incidence in levetiracetam-treated patients is ≥5% more than in placebo-treated patients) include: somnolence, asthenia, infection, and dizziness (6.1)

To report SUSPECTED ADVERSE REACTIONS, contact WG Critical Care, LLC at 1-866-562-4708 or FDA at 1-800-FDA-1088 or www.fda.gov/medwatch.

8 USE IN SPECIFIC POPULATIONS

- Pregnancy: Plasma levels of levetiracetam may be decreased; monitor closely during pregnancy. Based on animal data, may cause fetal harm. (5.9, 8.1)

FULL PRESCRIBING INFORMATION

1 INDICATIONS AND USAGE

1.1 Partial-Onset Seizures

Levetiracetam in Sodium Chloride Injection is indicated as adjunctive therapy in the treatment of partial-onset seizures in adults with epilepsy.

1.2 Myoclonic Seizures in Patients with Juvenile Myoclonic Epilepsy

Levetiracetam in Sodium Chloride Injection is indicated as adjunctive therapy in the treatment of myoclonic seizures in adults with juvenile myoclonic epilepsy.

1.3 Primary Generalized Tonic-Clonic Seizures

Levetiracetam in Sodium Chloride Injection is indicated as adjunctive therapy in the treatment of primary generalized tonic-clonic seizures in adults with idiopathic generalized epilepsy.

1.4 Limitations of Use

Levetiracetam in Sodium Chloride Injection is an antiepileptic drug indicated for adult patients (16 years and older) when oral administration is temporarily not feasible.

2 DOSAGE AND ADMINISTRATION

2.1 General Information – Administration

Levetiracetam in Sodium Chloride Injection is for intravenous infusion only. It is available in the following concentrations: three single-dose 100 mL bags, each containing a different total dosage of levetiracetam (500 mg [5 mg/mL], 1000 mg [10 mg/mL], or 1500 mg [15 mg/mL]).

A single-dose bag should be administered intravenously over a 15-minute IV infusion period.

Parenteral drug products should be inspected visually for particulate matter and discoloration prior to administration whenever solution and container permit.

Levetiracetam in Sodium Chloride Injection should not be further diluted prior to use. Any unused portion of the Levetiracetam in Sodium Chloride Injection contents should be discarded.

2.2 Initial Exposure to Levetiracetam

Levetiracetam can be initiated with either intravenous or oral administration.

Partial-Onset Seizures

In clinical trials of oral levetiracetam, daily doses of 1000 mg, 2000 mg, and 3000 mg, given as twice-daily dosing, were shown to be effective. Although in some studies there was a tendency toward greater response with higher dose [see Clinical Studies (14.1)], a consistent increase in response with increased dose has not been shown.

Treatment should be initiated with a daily dose of 1000 mg/day, given as twice-daily dosing (500 mg twice daily). Additional dosing increments may be given (1000 mg/day additional every 2 weeks) to a maximum recommended daily dose of 3000 mg. Doses greater than 3000 mg/day have been used in open-label studies with levetiracetam tablets for periods of 6 months and longer. There is no evidence that doses greater than 3000 mg/day confer additional benefit.

Myoclonic Seizures in Patients with Juvenile Myoclonic Epilepsy

Treatment should be initiated with a dose of 1000 mg/day, given as twice-daily dosing (500 mg twice daily). Dosage should be increased by 1000 mg/day every 2 weeks to the recommended daily dose of 3000 mg. The effectiveness of doses lower than 3000 mg/day has not been studied.

Primary Generalized Tonic-Clonic Seizures

Treatment should be initiated with a dose of 1000 mg/day, given as twice-daily dosing (500 mg twice daily). Dosage should be increased by 1000 mg/day every 2 weeks to the recommended daily dose of 3000 mg. The effectiveness of doses lower than 3000 mg/day has not been adequately studied.

2.3 Switching to Intravenous Dosing

When switching from oral levetiracetam, the initial total daily intravenous dosage of levetiracetam should be equivalent to the total daily dosage and frequency of oral levetiracetam.

2.4 Switching to Oral Dosing

At the end of the intravenous treatment period, the patient may be switched to levetiracetam oral administration at the equivalent daily dosage and frequency of the intravenous administration.

2.5 Adult Patients with Impaired Renal Function

Levetiracetam dosing must be individualized according to the patient's renal function status. Recommended doses and adjustment for dose for adults are shown in Table 1. To use this dosing table, an estimate of the patient's creatinine clearance (CLcr) in mL/min is needed.

Table 1: Dosing Adjustment Regimen for Adult Patients with Impaired Renal Function
Group | Creatinine Clearance (mL/min) | Dosage (mg) | Frequency
Normal | greater than 80 | 500 to 1,500 | Every 12 hours
Mild | 50 to 80 | 500 to 1,000 | Every 12 hours
Moderate | 30 to 50 | 250 to 750 | Every 12 hours
Severe | less than 30 | 250 to 500 | Every 12 hours
ESRD patients using dialysis | ---- | 500 to 1,000 | [Following dialysis, a 250 mg to 500 mg supplemental dose is recommended.] Every 24 hours

2.6 Compatibility with Other Antiepileptic Drugs

Levetiracetam in Sodium Chloride Injection is found to be physically compatible and chemically stable for at least 24 hours when mixed with lorazepam, diazepam, and valproate sodium and stored at controlled room temperature 15°C to 30°C (59°F to 86°F).

There are no data to support the physical compatibility of levetiracetam injection with antiepileptic drugs that are not listed above.

2.7 Discontinuation of Levetiracetam

Avoid abrupt withdrawal from levetiracetam in order to reduce the risk of increased seizure frequency and status epilepticus [see Warnings and Precautions (5.7)].

3 DOSAGE FORMS AND STRENGTHS

Injection: Levetiracetam in Sodium Chloride Injection is a clear, colorless solution packaged in a single-dose bag and available in three strengths:

- 500 mg/100 mL (5 mg/mL): 500 mg levetiracetam in 0.82% sodium chloride
- 1000 mg/100 mL (10 mg/mL): 1000 mg levetiracetam in 0.75% sodium chloride
- 1500 mg/100 mL (15 mg/mL): 1500 mg levetiracetam in 0.54% sodium chloride

4 CONTRAINDICATIONS

Levetiracetam in Sodium Chloride Injection is contraindicated in patients with a hypersensitivity to levetiracetam. Reactions have included anaphylaxis and angioedema [see Warnings and Precautions (5.3)].

5 WARNINGS AND PRECAUTIONS

5.1 Psychiatric Reactions

In some patients levetiracetam causes behavioral abnormalities. The incidences of behavioral abnormalities in the myoclonic and primary generalized tonic-clonic seizure studies were comparable to those of the adult partial-onset seizure studies.

A total of 13.3% of adult levetiracetam-treated patients compared to 6.2% of placebo patients experienced non-psychotic behavioral symptoms (reported as aggression, agitation, anger, anxiety, apathy, depersonalization, depression, emotional lability, hostility, irritability, and nervousness).

A total of 1.7% of adult levetiracetam-treated patients discontinued treatment due to behavioral adverse events, compared to 0.2% of placebo patients. The treatment dose was reduced in 0.8% of adult levetiracetam-treated patients and in 0.5% of placebo patients.

One percent of adult levetiracetam-treated patients experienced psychotic symptoms compared to 0.2% of placebo patients.

Two (0.3%) adult levetiracetam-treated patients were hospitalized and their treatment was discontinued due to psychosis. Both events, reported as psychosis, developed within the first week of treatment and resolved within 1 to 2 weeks following treatment discontinuation.

The above psychiatric signs and symptoms should be monitored.

5.2 Somnolence and Fatigue

In some patients, levetiracetam causes somnolence and fatigue. The incidences of somnolence and fatigue provided below are from controlled adult partial-onset seizure studies. In general, the incidences of somnolence and fatigue in the myoclonic and primary generalized tonic-clonic studies were comparable to those of the adult partial-onset seizure studies.

In controlled trials of adult patients with epilepsy experiencing partial-onset seizures, 14.8% of levetiracetam-treated patients reported somnolence, compared to 8.4% of placebo patients. There was no clear dose response up to 3000 mg/day. In a study where there was no titration, about 45% of patients receiving 4000 mg/day reported somnolence. The somnolence was considered serious in 0.3% of the treated patients, compared to 0% in the placebo group. About 3% of levetiracetam-treated patients discontinued treatment due to somnolence, compared to 0.7% of placebo patients. In 1.4% of treated patients and in 0.9% of placebo patients the dose was reduced, while 0.3% of the treated patients were hospitalized due to somnolence.

In controlled trials of adult patients with epilepsy experiencing partial-onset seizures, 14.7% of levetiracetam-treated patients reported asthenia, compared to 9.1% of placebo patients. Treatment was discontinued due to asthenia in 0.8% of treated patients as compared to 0.5% of placebo patients. In 0.5% of treated patients and in 0.2% of placebo patients the dose was reduced due to asthenia.

Somnolence and asthenia occurred most frequently within the first 4 weeks of treatment.

Patients should be monitored for these signs and symptoms and advised not to drive or operate machinery until they have gained sufficient experience on levetiracetam to gauge whether it adversely affects their ability to drive or operate machinery.

5.3 Anaphylaxis and Angioedema

Levetiracetam can cause anaphylaxis or angioedema after the first dose or at any time during treatment. Signs and symptoms in cases reported in the postmarketing setting with levetiracetam have included hypotension, hives, rash, respiratory distress, and swelling of the face, lip, mouth, eye, tongue, throat, and feet. In some reported cases, reactions were life-threatening and required emergency treatment. If a patient develops signs or symptoms of anaphylaxis or angioedema, levetiracetam should be discontinued and the patient should seek immediate medical attention. Levetiracetam should be discontinued permanently if a clear alternative etiology for the reaction cannot be established [see Contraindications (4)].

5.4 Serious Dermatological Reactions

Serious dermatological reactions, including Stevens-Johnson syndrome (SJS) and toxic epidermal necrolysis (TEN), have been reported in patients treated with levetiracetam. The median time of onset is reported to be 14 to 17 days, but cases have been reported at least four months after initiation of treatment. Recurrence of the serious skin reactions following rechallenge with levetiracetam has also been reported. Levetiracetam should be discontinued at the first sign of a rash, unless the rash is clearly not drug-related. If signs or symptoms suggest SJS/TEN, use of this drug should not be resumed and alternative therapy should be considered.

5.5 Drug Reaction with Eosinophilia and Systemic Symptoms (DRESS)/Multiorgan Hypersensitivity

Drug Reaction with Eosinophilia and Systemic Symptoms (DRESS), also known as multiorgan hypersensitivity, has been reported in patients taking antiepileptic drugs, including levetiracetam. These events can be fatal or life-threatening, particularly if diagnosis and treatment do not occur as early as possible. DRESS typically, although not exclusively, presents with fever, rash, lymphadenopathy, and/or facial swelling, in association with other organ system involvement, such as hepatitis, nephritis, hematological abnormalities, myocarditis, or myositis, sometimes resembling an acute viral infection. Eosinophilia is often present. Because this disorder is variable in its expression, other organ systems not noted here may be involved. It is important to note that early manifestations of hypersensitivity, such as fever or lymphadenopathy, may be present even though rash is not evident. If such signs or symptoms are present, the patient should be evaluated immediately. Levetiracetam should be discontinued if an alternative etiology for the signs or symptoms cannot be established [see Contraindications (4)].

5.6 Coordination Difficulties

Coordination difficulties were only observed in the adult partial-onset seizure studies. A total of 3.4% of adult levetiracetam-treated patients experienced coordination difficulties, (reported as either ataxia, abnormal gait, or incoordination) compared to 1.6% of placebo patients. A total of 0.4% of patients in controlled trials discontinued levetiracetam treatment due to ataxia, compared to 0% of placebo patients. In 0.7% of treated patients and in 0.2% of placebo patients the dose was reduced due to coordination difficulties, while one of the treated patients was hospitalized due to worsening of pre-existing ataxia. These events occurred most frequently within the first 4 weeks of treatment.

Patients should be monitored for these signs and symptoms and advised not to drive or operate machinery until they have gained sufficient experience on levetiracetam to gauge whether it adversely affects their ability to drive or operate machinery.

5.7 Withdrawal Seizures

As with most antiepileptic drugs, levetiracetam should be withdrawn gradually because of the risk of increased seizure frequency and status epilepticus. But if withdrawal is needed because of a serious adverse reaction, rapid discontinuation can be considered.

5.8 Hematologic Abnormalities

Levetiracetam can cause hematologic abnormalities. Hematologic abnormalities occurred in clinical trials and included decreases in white blood cell (WBC), neutrophil, and red blood cells counts (RBC); decreases in hemoglobin and hematocrit; and increases in eosinophil counts. Cases of agranulocytosis, pancytopenia, and thrombocytopenia have been reported in the postmarketing setting. A complete blood count is recommended in patients experiencing significant weakness, pyrexia, recurrent infections, or coagulation disorders.

Partial-Onset Seizures

In controlled clinical studies using an oral formulation of levetiracetam in adult patients with partial-onset seizures, minor but statistically significant decreases compared to placebo in total mean RBC (0.03 × 10^6/mm^3), mean hemoglobin (0.09 g/dL), and mean hematocrit (0.38%), were seen in levetiracetam-treated patients.

A total of 3.2% of levetiracetam-treated and 1.8% of placebo-treated patients had at least one possibly significant (≤2.8 × 10^9/L) decreased WBC, and 2.4% of levetiracetam-treated and 1.4% of placebo-treated patients had at least one possibly significant (≤1.0 × 10^9/L) decreased neutrophil count. Of the levetiracetam-treated patients with a low neutrophil count, all but one rose towards or to baseline with continued treatment. No patient was discontinued secondary to low neutrophil counts.

Juvenile Myoclonic Epilepsy

Although there were no obvious hematologic abnormalities observed in patients with JME, the limited number of patients makes any conclusion tentative. The data from the partial seizure patients should be considered to be relevant for JME patients.

5.9 Seizure Control During Pregnancy

Physiological changes may gradually decrease plasma levels of levetiracetam throughout pregnancy. This decrease is more pronounced during the third trimester. It is recommended that patients be monitored carefully during pregnancy. Close monitoring should continue through the postpartum period especially if the dose was changed during pregnancy.

6 ADVERSE REACTIONS

The following serious adverse reactions are discussed in more details in other sections of labeling:

- Psychiatric Reactions [see Warnings and Precautions (5.1)]
- Somnolence and Fatigue [see Warnings and Precautions (5.2)]
- Anaphylaxis and Angioedema [see Warnings and Precautions (5.3)]
- Serious Dermatological Reactions [see Warnings and Precautions (5.4)]
- Drug Reaction with Eosinophilia and Systemic Symptoms (DRESS)/Multiorgan Hypersensitivity [see Warnings and Precautions (5.5)]
- Coordination Difficulties [see Warnings and Precautions (5.6)]
- Withdrawal Seizures [see Warnings and Precautions (5.7)]
- Hematologic Abnormalities [see Warnings and Precautions (5.8)]
- Seizure Control During Pregnancy [see Warnings and Precautions (5.9)]

6.1 Clinical Trials Experience

Because clinical trials are conducted under widely varying conditions, adverse reaction rates observed in the clinical trials of a drug cannot be directly compared to rates in the clinical trials of another drug and may not reflect the rates observed in practice.

The adverse reactions that result from levetiracetam injection use include all of those reported for levetiracetam tablets and oral solution. Equivalent doses of intravenous (IV) levetiracetam and oral levetiracetam result in equivalent Cmax, Cmin, and total systemic exposure to levetiracetam when the IV levetiracetam is administered as a 15-minute infusion.

Partial-Onset Seizures

In controlled clinical studies using levetiracetam tablets in adults with partial-onset seizures [see Clinical Studies (14.1)], the most common adverse reactions in adult patients receiving levetiracetam in combination with other AEDs, for events with rates greater than placebo, were somnolence, asthenia, infection and dizziness.

Of the most common adverse reactions in adults experiencing partial-onset seizures, asthenia, somnolence and dizziness occurred predominantly during the first 4 weeks of treatment with levetiracetam.

Table 2 lists adverse reactions that occurred in at least 1% of adult epilepsy patients receiving levetiracetam tablets in placebo-controlled studies and were numerically more common than in patients treated with placebo. In these studies, either levetiracetam or placebo was added to concurrent AED therapy. Adverse reactions were usually mild to moderate in intensity.

Table 2: Adverse Reactions [Adverse reactions occurred in at least 1% of levetiracetam-treated patients and occurred more frequently than placebo-treated patients] In Placebo-Controlled, Adjunctive Studies In Adults Experiencing Partial-Onset Seizures
Adverse Reaction | Levetiracetam (N=769); % | Placebo (N=439); %
Asthenia | 15 | 9
Somnolence | 15 | 8
Headache | 14 | 13
Infection | 13 | 8
Dizziness | 9 | 4
Pain | 7 | 6
Pharyngitis | 6 | 4
Depression | 4 | 2
Nervousness | 4 | 2
Rhinitis | 4 | 3
Anorexia | 3 | 2
Ataxia | 3 | 1
Vertigo | 3 | 1
Amnesia | 2 | 1
Anxiety | 2 | 1
Cough Increased | 2 | 1
Diplopia | 2 | 1
Emotional Lability | 2 | 0
Hostility | 2 | 1
Paresthesia | 2 | 1
Sinusitis | 2 | 1

In controlled adult clinical studies using levetiracetam tablets, 15% of patients receiving levetiracetam and 12% receiving placebo either discontinued or had a dose reduction as a result of an adverse reaction. Table 3 lists the most common (>1%) adverse reactions that resulted in discontinuation or dose reduction and that occurred more frequently in levetiracetam-treated patients than in placebo-treated patients.

Table 3: Adverse Reactions that Resulted in Discontinuation or Dose Reduction in Placebo-Controlled Studies in Adults Experiencing Partial-Onset Seizures
Adverse Reaction | Levetiracetam (N=769) % | Placebo (N=439) %
Somnolence | 4 | 2
Dizziness | 1 | 0

Myoclonic Seizures

Although the pattern of adverse reactions in this study seems somewhat different from that seen in patients with partial seizures, this is likely due to the much smaller number of patients in this study compared to partial seizure studies. The adverse reaction pattern for patients with JME is expected to be essentially the same as for patients with partial seizures.

In the controlled clinical study using levetiracetam tablets in patients with myoclonic seizures, the most common adverse reactions in patients using levetiracetam in combination with other AEDs, for events with rates greater than placebo, were somnolence, neck pain, and pharyngitis.

Table 4 lists adverse reactions that occurred in at least 5% of juvenile myoclonic epilepsy patients experiencing myoclonic seizures treated with levetiracetam tablets and were numerically more common than in patients treated with placebo. In this study, either levetiracetam or placebo was added to concurrent AED therapy. Adverse reactions were usually mild to moderate in intensity.

Table 4: Adverse Reactions [Adverse reactions occurred in at least 5% of levetiracetam-treated patients and occurred more frequently than placebo-treated patients] in a Placebo-Controlled, Adjunctive Study in Patients 12 Years of Age and Older with Myoclonic Seizures
Adverse Reaction | Levetiracetam (N=60) % | Placebo (N=60) %
Somnolence | 12 | 2
Neck pain | 8 | 2
Pharyngitis | 7 | 0
Depression | 5 | 2
Influenza | 5 | 2
Vertigo | 5 | 3

In the placebo-controlled study using levetiracetam tablets in patients with JME, 8% of patients receiving levetiracetam and 2% receiving placebo either discontinued or had a dose reduction as a result of an adverse reaction. The adverse reactions that led to discontinuation or dose reduction and that occurred more frequently in levetiracetam-treated patients than in placebo-treated patients are presented in Table 5.

Table 5: Adverse Reactions that Resulted in Discontinuation or Dose Reduction in Patients with Juvenile Myoclonic Epilepsy
Adverse Reaction | Levetiracetam (N=60) % | Placebo (N=60) %
Anxiety | 3 | 2
Depressed mood | 2 | 0
Depression | 2 | 0
Diplopia | 2 | 0
Hypersomnia | 2 | 0
Insomnia | 2 | 0
Irritability | 2 | 0
Nervousness | 2 | 0
Somnolence | 2 | 0

Primary Generalized Tonic-Clonic Seizures

Although the pattern of adverse reactions in this study seems somewhat different from that seen in patients with partial seizures, this is likely due to the much smaller number of patients in this study compared to partial seizure studies. The adverse reaction pattern for patients with primary generalized tonic-clonic (PGTC) seizures is expected to be essentially the same as for patients with partial seizures.

In the controlled clinical study that included patients with PGTC seizures, the most common adverse reaction in patients receiving levetiracetam oral formulation in combination with other AEDs, for events with rates greater than placebo was nasopharyngitis.

Table 6 lists adverse reactions that occurred in at least 5% of idiopathic generalized epilepsy patients experiencing PGTC seizures treated with levetiracetam and were numerically more common than in patients treated with placebo. In this study, either levetiracetam or placebo was added to concurrent AED therapy.

Table 6: Adverse Reactions [Adverse reactions occurred in at least 5% of levetiracetam-treated patients and occurred more frequently than placebo-treated patients] in a Placebo-Controlled, Adjunctive Study in Patients with PGTC Seizures
Adverse Reaction | Levetiracetam (N=79) % | Placebo (N=84) %
Nasopharyngitis | 14 | 5
Fatigue | 10 | 8
Diarrhea | 8 | 7
Irritability | 6 | 2
Mood swings | 5 | 1

In the placebo-controlled study, 5% of patients receiving levetiracetam and 8% receiving placebo either discontinued or had a dose reduction during the treatment period as a result of an adverse reaction.

This study was too small to adequately characterize the adverse reactions that could be expected to result in discontinuation of treatment in this population. It is expected that the adverse reactions that would lead to discontinuation in this population would be similar to those resulting in discontinuation in other epilepsy trials (see Tables 3 and 5).

In addition, the following adverse reactions were seen in other controlled adult studies of levetiracetam: balance disorder, disturbance in attention, eczema, memory impairment, myalgia, and blurred vision.

Comparison of Gender, Age and Race

The overall adverse reaction profile of levetiracetam was similar between females and males. There are insufficient data to support a statement regarding the distribution of adverse reactions by age and race.

6.2 Postmarketing Experience

The following adverse reactions have been identified during post-approval use of levetiracetam. Because these reactions are reported voluntarily from a population of uncertain size, it is not always possible to reliably estimate their frequency or establish a causal relationship to drug exposure.

In addition to the adverse reactions listed above [see Adverse Reactions (6.1)], the following adverse reactions have been reported in patients receiving marketed levetiracetam worldwide. The listing is alphabetized: abnormal liver function test, acute kidney injury, agranulocytosis, anaphylaxis, angioedema, choreoathetosis, drug reaction with eosinophilia and systemic symptoms (DRESS), dyskinesia, erythema multiforme, hepatic failure, hepatitis, hyponatremia, muscular weakness, obsessive compulsive disorders (OCD), pancreatitis, pancytopenia (with bone marrow suppression identified in some of these cases), panic attack, thrombocytopenia, weight loss, and worsening of seizures including in patients with SCN8A mutations. Alopecia has been reported with levetiracetam use; recovery was observed in majority of cases where levetiracetam was discontinued.

8 USE IN SPECIFIC POPULATIONS

8.1 Pregnancy

Pregnancy Exposure Registry

There is a pregnancy exposure registry that monitors pregnancy outcomes in women exposed to antiepileptic drugs (AEDs), including levetiracetam, during pregnancy. Encourage women who are taking levetiracetam injection during pregnancy to enroll in the North American Antiepileptic Drug (NAAED) pregnancy registry by calling 1-888-233-2334 or visiting http://www.aedpregnancyregistry.org/.

Risk Summary

Prolonged experience with levetiracetam in pregnant women has not identified a drug-associated risk of major birth defects or miscarriage, based on published literature, which includes data from pregnancy registries and reflects experience over two decades [see Human Data]. In animal studies, levetiracetam produced developmental toxicity (increased embryofetal and offspring mortality, increased incidences of fetal structural abnormalities, decreased embryofetal and offspring growth, neurobehavioral alterations in offspring) at doses similar to human therapeutic doses [see Animal Data].

In the U.S. general population, the estimated background risk of major birth defects and miscarriage in clinically recognized pregnancies is 2-4% and 15-20%, respectively. The background risk of major birth defects and miscarriage for the indicated population is unknown.

Clinical Considerations

Levetiracetam blood levels may decrease during pregnancy [see Warnings and Precautions (5.9)].

Physiological changes during pregnancy may affect levetiracetam concentration. Decrease in levetiracetam plasma concentrations has been observed during pregnancy. This decrease is more pronounced during the third trimester. Dose adjustments may be necessary to maintain clinical response.

Data

Human Data

While available studies cannot definitively establish the absence of risk, data from the published literature and pregnancy registries have not established an association with levetiracetam use during pregnancy and major birth defects or miscarriage.

Animal Data

When levetiracetam (0, 400, 1200, or 3600 mg/kg/day) was administered orally to pregnant rats during the period of organogenesis, reduced fetal weights and increased incidence of fetal skeletal variations were observed at the highest dose tested. There was no evidence of maternal toxicity. The no-effect dose for adverse effects on embryofetal development in rats (1200 mg/kg/day) is approximately 4 times the maximum recommended human dose (MRHD) of 3000 mg on a body surface area (mg/m^2) basis.

Oral administration of levetiracetam (0, 200, 600, or 1800 mg/kg/day) to pregnant rabbits during the period of organogenesis resulted in increased embryofetal mortality and incidence of fetal skeletal variations at the mid and high dose and decreased fetal weights and increased incidence of fetal malformations at the high dose, which was associated with maternal toxicity. The no-effect dose for adverse effects on embryofetal development in rabbits (200 mg/kg/day) is approximately equivalent to the MRHD on a mg/m^2 basis.

Oral administration of levetiracetam (0, 70, 350, or 1800 mg/kg/day) to female rats throughout pregnancy and lactation led to an increased incidence of fetal skeletal variations, reduced fetal body weight, and decreased growth in offspring at the mid and high doses and increased pup mortality and neurobehavioral alterations in offspring at the highest dose tested. There was no evidence of maternal toxicity. The no-effect dose for adverse effects on pre- and postnatal development in rats (70 mg/kg/day) is less than the MRHD on a mg/m^2 basis.

Oral administration of levetiracetam to rats during the latter part of gestation and throughout lactation produced no adverse developmental or maternal effects at doses of up to 1800 mg/kg/day (6 times the MRHD on a mg/m^2 basis).

8.2 Lactation

Risk Summary

Levetiracetam is excreted in human milk. There are no data on the effects of levetiracetam on the breastfed infant, or the effects on milk production.

The development and health benefits of breastfeeding should be considered along with the mother’s clinical need for levetiracetam and any potential adverse effects on the breastfed infant from levetiracetam or from the underlying maternal condition.

8.4 Pediatric Use

Safety and effectiveness of levetiracetam injection in patients below the age of 16 years have not been established.

8.5 Geriatric Use

There were 347 subjects in clinical studies of levetiracetam that were 65 years old and over. No overall differences in safety were observed between these subjects and younger subjects. There were insufficient numbers of elderly subjects in controlled trials of epilepsy to adequately assess the effectiveness of levetiracetam in these patients.

Levetiracetam is known to be substantially excreted by the kidney, and the risk of adverse reactions to this drug may be greater in patients with impaired renal function. Because elderly patients are more likely to have decreased renal function, care should be taken in dose selection, and it may be useful to monitor renal function [see Clinical Pharmacology (12.3)].

8.6 Renal Impairment

Clearance of levetiracetam is decreased in patients with renal impairment and is correlated with creatinine clearance [see Clinical Pharmacology (12.3)]. Dosage adjustment is recommended for patients with impaired renal function and supplemental doses should be given to patients after dialysis [see Dosage and Administration (2.5)].

10 OVERDOSAGE

10.1 Signs, Symptoms and Laboratory Findings of Acute Overdosage in Humans

The highest known dose of oral levetiracetam received in the clinical development program was 6000 mg/day. Other than drowsiness, there were no adverse reactions in the few known cases of overdose in clinical trials. Cases of somnolence, agitation, aggression, depressed level of consciousness, respiratory depression and coma were observed with levetiracetam overdoses in postmarketing use.

10.2 Management of Overdose

There is no specific antidote for overdose with levetiracetam. If indicated, elimination of unabsorbed drug should be attempted by emesis or gastric lavage; usual precautions should be observed to maintain airway. General supportive care of the patient is indicated including monitoring of vital signs and observation of the patient’s clinical status. A Certified Poison Control Center should be contacted for up to date information on the management of overdose with levetiracetam.

10.3 Hemodialysis

Standard hemodialysis procedures result in significant clearance of levetiracetam (approximately 50% in 4 hours) and should be considered in cases of overdose. Although hemodialysis has not been performed in the few known cases of overdose, it may be indicated by the patient's clinical state or in patients with significant renal impairment.

11 DESCRIPTION

Levetiracetam in Sodium Chloride Injection is an antiepileptic drug available as a clear, colorless, sterile solution for intravenous administration.

The chemical name of levetiracetam, a single enantiomer, is (-)-(S)-α-ethyl-2-oxo-1-pyrrolidine acetamide, its molecular formula is C8H14N2O2 and its molecular weight is 170.21. Levetiracetam is chemically unrelated to existing antiepileptic drugs (AEDs). It has the following structural formula:

Levetiracetam is a white to off-white crystalline powder with a faint odor and a bitter taste. It is very soluble in water (104.0 g/100 mL). It is freely soluble in chloroform (65.3 g/100 mL) and in methanol (53.6 g/100 mL), soluble in ethanol (16.5 g/100 mL), sparingly soluble in acetonitrile (5.7 g/100 mL) and practically insoluble in n-hexane. (Solubility limits are expressed as g/100 mL solvent.)

Levetiracetam in Sodium Chloride Injection is a clear, colorless, sterile solution that is available in a single-dose dual port bag with an aluminum overwrap. The container closure is not made with natural rubber latex.

500 mg/100 mL: One 100 mL bag contains 500 mg of levetiracetam (5 mg/mL), water for injection, 820 mg sodium chloride, 5.5 mg of glacial acetic acid and buffered at approximately pH 5.5 with glacial acetic acid and 164 mg sodium acetate trihydrate.

1000 mg/100 mL: One 100 mL bag contains 1000 mg of levetiracetam (10 mg/mL), water for injection, 750 mg sodium chloride, 6.5 mg of glacial acetic acid and buffered at approximately pH 5.5 with glacial acetic acid and 164 mg sodium acetate trihydrate.

1500 mg/100 mL: One 100 mL bag contains 1500 mg of levetiracetam (15 mg/mL), water for injection, 540 mg sodium chloride, 7.5 mg of glacial acetic acid and buffered at approximately pH 5.5 with glacial acetic acid and 164 mg sodium acetate trihydrate.

12 CLINICAL PHARMACOLOGY

12.1 Mechanism of Action

The precise mechanism(s) by which levetiracetam exerts its antiepileptic effect is unknown.

A saturable and stereoselective neuronal binding site in rat brain tissue has been described for levetiracetam. Experimental data indicate that this binding site is the synaptic vesicle protein SV2A, thought to be involved in the regulation of vesicle exocytosis. Although the molecular significance of levetiracetam binding to synaptic vesicle protein SV2A is not understood, levetiracetam and related analogs showed a rank order of affinity for SV2A which correlated with the potency of their antiseizure activity in audiogenic seizure-prone mice. These findings suggest that the interaction of levetiracetam with the SV2A protein may contribute to the antiepileptic mechanism of action of the drug.

12.2 Pharmacodynamics

Effects on QTc Interval

The effect of levetiracetam on QTc prolongation was evaluated in a randomized, double-blind, positive-controlled (moxifloxacin 400 mg) and placebo-controlled crossover study of levetiracetam (1000 mg or 5000 mg) in 52 healthy subjects. The upper bound of the 90% confidence interval for the largest placebo-adjusted, baseline-corrected QTc was below 10 milliseconds. Therefore, there was no evidence of significant QTc prolongation in this study.

12.3 Pharmacokinetics

Equivalent doses of intravenous (IV) levetiracetam and oral levetiracetam result in equivalent Cmax, Cmin, and total systemic exposure to levetiracetam when the IV levetiracetam is administered as a 15 minute infusion.

Overview

Levetiracetam is rapidly and almost completely absorbed after oral administration. Levetiracetam injection and tablets are bioequivalent. The pharmacokinetics of levetiracetam are linear and time-invariant, with low intra- and inter-subject variability. Levetiracetam is not significantly protein-bound (<10% bound) and its volume of distribution is close to the volume of intracellular and extracellular water. Sixty-six percent (66%) of the dose is renally excreted unchanged. The major metabolic pathway of levetiracetam (24% of dose) is an enzymatic hydrolysis of the acetamide group. It is not liver cytochrome P450 dependent. The metabolites have no known pharmacological activity and are renally excreted. Plasma half-life of levetiracetam across studies is approximately 6-8 hours. It is increased in the elderly (primarily due to impaired renal clearance) and in subjects with renal impairment.

Distribution

The equivalence of levetiracetam injection and the oral formulation was demonstrated in a bioavailability study of 17 healthy volunteers. In this study, levetiracetam 1500 mg was diluted in 100 mL 0.9% sterile saline solution and was infused over 15 minutes. The selected infusion rate provided plasma concentrations of levetiracetam at the end of the infusion period similar to those achieved at Tmax after an equivalent oral dose. It is demonstrated that levetiracetam 1500 mg intravenous infusion is equivalent to levetiracetam 3 x 500 mg oral tablets. The time independent pharmacokinetic profile of levetiracetam was demonstrated following 1500 mg intravenous infusion for 4 days with BID dosing. The AUC(0-12) at steady-state was equivalent to AUCinf following an equivalent single dose.

Levetiracetam and its major metabolite are less than 10% bound to plasma proteins; clinically significant interactions with other drugs through competition for protein binding sites are therefore unlikely.

Metabolism

Levetiracetam is not extensively metabolized in humans. The major metabolic pathway is the enzymatic hydrolysis of the acetamide group, which produces the carboxylic acid metabolite, ucb L057 (24% of dose) and is not dependent on any liver cytochrome P450 isoenzymes. The major metabolite is inactive in animal seizure models. Two minor metabolites were identified as the product of hydroxylation of the 2-oxo-pyrrolidine ring (2% of dose) and opening of the 2-oxo-pyrrolidine ring in position 5 (1% of dose). There is no enantiomeric interconversion of levetiracetam or its major metabolite.

Elimination

Levetiracetam plasma half-life in adults is 7 ± 1 hour and is unaffected by either dose, route of administration or repeated administration. Levetiracetam is eliminated from the systemic circulation by renal excretion as unchanged drug which represents 66% of administered dose. The total body clearance is 0.96 mL/min/kg and the renal clearance is 0.6 mL/min/kg. The mechanism of excretion is glomerular filtration with subsequent partial tubular reabsorption. The metabolite ucb L057 is excreted by glomerular filtration and active tubular secretion with a renal clearance of 4 mL/min/kg. Levetiracetam elimination is correlated to creatinine clearance. Levetiracetam clearance is reduced in patients with renal impairment [see Dosage and Administration (2.5) and Use in Specific Populations (8.6)].

Specific Populations

Elderly

Pharmacokinetics of levetiracetam were evaluated in 16 elderly subjects (age 61-88 years) with creatinine clearance ranging from 30 to 74 mL/min. Following oral administration of twice-daily dosing for 10 days, total body clearance decreased by 38% and the half-life was 2.5 hours longer in the elderly compared to healthy adults. This is most likely due to the decrease in renal function in these subjects.

Pregnancy

Levetiracetam levels may decrease during pregnancy [see Warnings and Precautions (5.9) and Use in Specific Populations (8.1)].

Gender

Levetiracetam Cmax and AUC were 20% higher in women (N=11) compared to men (N=12). However, clearances adjusted for body weight were comparable.

Race

Formal pharmacokinetic studies of the effects of race have not been conducted. Cross study comparisons involving Caucasians (N=12) and Asians (N=12), however, show that pharmacokinetics of levetiracetam were comparable between the two races. Because levetiracetam is primarily renally excreted and there are no important racial differences in creatinine clearance, pharmacokinetic differences due to race are not expected.

Renal Impairment

The disposition of levetiracetam was studied in adult subjects with varying degrees of renal function. Total body clearance of levetiracetam is reduced in patients with impaired renal function by 40% in the mild group (CLcr = 50-80 mL/min), 50% in the moderate group (CLcr = 30-50 mL/min) and 60% in the severe renal impairment group (CLcr <30 mL/min). Clearance of levetiracetam is correlated with creatinine clearance.

In anuric (end stage renal disease) patients, the total body clearance decreased 70% compared to normal subjects (CLcr >80mL/min). Approximately 50% of the pool of levetiracetam in the body is removed during a standard 4 hour hemodialysis procedure [see Dosage and Administration (2.5)].

Hepatic Impairment

In subjects with mild (Child-Pugh A) to moderate (Child-Pugh B) hepatic impairment, the pharmacokinetics of levetiracetam were unchanged. In patients with severe hepatic impairment (Child-Pugh C), total body clearance was 50% that of normal subjects, but decreased renal clearance accounted for most of the decrease. No dose adjustment is needed for patients with hepatic impairment.

Drug Interactions

In vitro data on metabolic interactions indicate that levetiracetam is unlikely to produce, or be subject to, pharmacokinetic interactions. Levetiracetam and its major metabolite, at concentrations well above Cmax levels achieved within the therapeutic dose range, are neither inhibitors of nor high affinity substrates for human liver cytochrome P450 isoforms, epoxide hydrolase or UDP-glucuronidation enzymes. In addition, levetiracetam does not affect the in vitro glucuronidation of valproic acid.

Potential pharmacokinetic interactions of or with levetiracetam were assessed in clinical pharmacokinetic studies (phenytoin, valproate, warfarin, digoxin, oral contraceptive, probenecid) and through pharmacokinetic screening in the placebo-controlled clinical studies in epilepsy patients.

Phenytoin

Levetiracetam (3000 mg daily) had no effect on the pharmacokinetic disposition of phenytoin in patients with refractory epilepsy. Pharmacokinetics of levetiracetam were also not affected by phenytoin.

Valproate

Levetiracetam (1500 mg twice daily) did not alter the pharmacokinetics of valproate in healthy volunteers. Valproate 500 mg twice daily did not modify the rate or extent of levetiracetam absorption or its plasma clearance or urinary excretion. There also was no effect on exposure to and the excretion of the primary metabolite, ucb L057.

Other Antiepileptic Drugs

Potential drug interactions between levetiracetam and other AEDs (carbamazepine, gabapentin, lamotrigine, phenobarbital, phenytoin, primidone and valproate) were also assessed by evaluating the serum concentrations of levetiracetam and these AEDs during placebo-controlled clinical studies. These data indicate that levetiracetam does not influence the plasma concentration of other AEDs and that these AEDs do not influence the pharmacokinetics of levetiracetam.

Oral Contraceptives

Levetiracetam (500 mg twice daily) did not influence the pharmacokinetics of an oral contraceptive containing 0.03 mg ethinyl estradiol and 0.15 mg levonorgestrel, or of the luteinizing hormone and progesterone levels, indicating that impairment of contraceptive efficacy is unlikely. Coadministration of this oral contraceptive did not influence the pharmacokinetics of levetiracetam.

Digoxin

Levetiracetam (1000 mg twice daily) did not influence the pharmacokinetics and pharmacodynamics (ECG) of digoxin given as a 0.25 mg dose every day. Coadministration of digoxin did not influence the pharmacokinetics of levetiracetam.

Warfarin

Levetiracetam (1000 mg twice daily) did not influence the pharmacokinetics of R and S warfarin. Prothrombin time was not affected by levetiracetam. Coadministration of warfarin did not affect the pharmacokinetics of levetiracetam.

Probenecid

Probenecid, a renal tubular secretion blocking agent, administered at a dose of 500 mg four times a day, did not change the pharmacokinetics of levetiracetam 1000 mg twice daily. Cssmax of the metabolite, ucb L057, was approximately doubled in the presence of probenecid while the fraction of drug excreted unchanged in the urine remained the same. Renal clearance of ucb L057 in the presence of probenecid decreased 60%, probably related to competitive inhibition of tubular secretion of ucb L057. The effect of levetiracetam on probenecid was not studied.

13 NONCLINICAL TOXICOLOGY

13.1 Carcinogenesis, Mutagenesis, Impairment of Fertility

Carcinogenesis

Rats were dosed with levetiracetam in the diet for 104 weeks at doses of 50, 300 and 1800 mg/kg/day. Plasma exposure (AUC) at the highest dose was approximately 6 times that in humans at the maximum recommended human dose (MRHD) of 3000 mg. There was no evidence of carcinogenicity. In mice, oral administration of levetiracetam for 80 weeks (doses up to 960 mg/kg/day) or 2 years (doses up to 4000 mg/kg/day, lowered to 3000 mg/kg/day after 45 weeks due to intolerability) was not associated with an increase in tumors. The highest dose tested in mice for 2 years (3000 mg/kg/day) is approximately 5 times the MRHD on a body surface area (mg/m^2) basis.

Mutagenesis

Levetiracetam was negative in in vitro (Ames, chromosomal aberration in mammalian cells) and in vivo (mouse micronucleus) assays. The major human metabolite of levetiracetam (ucb L057) was negative in in vitro (Ames, mouse lymphoma) assays.

Impairment of Fertility

No adverse effects on male or female fertility or reproductive performance were observed in rats at oral doses up to 1800 mg/kg/day, which were associated with plasma exposures (AUC) up to approximately 6 times that in humans at the MRHD.

14 CLINICAL STUDIES

All clinical studies supporting the efficacy of levetiracetam utilized oral formulations. The finding of efficacy of levetiracetam injection is based on the results of studies using an oral formulation of levetiracetam, and on the demonstration of comparable bioavailability of the oral and parenteral formulations [see Pharmacokinetics (12.3)].

14.1 Partial-Onset Seizures

The effectiveness of levetiracetam as adjunctive therapy (added to other antiepileptic drugs) in adults was established in three multicenter, randomized, double-blind, placebo-controlled clinical studies in patients who had refractory partial-onset seizures with or without secondary generalization. The tablet formulation was used in all these studies. In these studies, 904 patients were randomized to placebo, 1000 mg, 2000 mg, or 3000 mg/day. Patients enrolled in Study 1 or Study 2 had refractory partial-onset seizures for at least two years and had taken two or more classical AEDs. Patients enrolled in Study 3 had refractory partial-onset seizures for at least 1 year and had taken one classical AED. At the time of the study, patients were taking a stable dose regimen of at least one and could take a maximum of two AEDs. During the baseline period, patients had to have experienced at least two partial-onset seizures during each 4-week period.

Study 1

Study 1 was a double-blind, placebo-controlled, parallel-group study conducted at 41 sites in the United States comparing levetiracetam 1000 mg/day (N=97), levetiracetam 3000 mg/day (N=101), and placebo (N=95) given in equally divided doses twice daily. After a prospective baseline period of 12 weeks, patients were randomized to one of the three treatment groups described above. The 18-week treatment period consisted of a 6-week titration period, followed by a 12-week fixed dose evaluation period, during which concomitant AED regimens were held constant. The primary measure of effectiveness was a between group comparison of the percent reduction in weekly partial seizure frequency relative to placebo over the entire randomized treatment period (titration + evaluation period). Secondary outcome variables included the responder rate (incidence of patients with ≥50% reduction from baseline in partial-onset seizure frequency). The results of the analysis of Study 1 are displayed in Table 7.

Table 7: Reduction in Mean Over Placebo in Weekly Frequency of Partial-Onset Seizures in Study 1
 | Placebo (N=95) | Levetiracetam 1000 mg/day (N=97) | Levetiracetam 3000 mg/day (N=101)
Percent reduction in partial seizure frequency over placebo | – | 26.1% [Statistically significant versus placebo] | 30.1%

The percentage of patients (y-axis) who achieved ≥50% reduction in weekly seizure rates from baseline in partial-onset seizure frequency over the entire randomized treatment period (titration + evaluation period) within the three treatment groups (x-axis) is presented in Figure 1.

*statistically significant versus placebo.

Figure 1: Responder Rate (≥50% Reduction from Baseline) in Study 1

Study 2

Study 2 was a double-blind, placebo-controlled, crossover study conducted at 62 centers in Europe comparing levetiracetam 1000 mg/day (N=106), levetiracetam 2000 mg/day (N=105), and placebo (N=111) given in equally divided doses twice daily.

The first period of the study (Period A) was designed to be analyzed as a parallel-group study. After a prospective baseline period of up to 12 weeks, patients were randomized to one of the three treatment groups described above. The 16-week treatment period consisted of the 4-week titration period followed by a 12-week fixed dose evaluation period, during which concomitant AED regimens were held constant. The primary measure of effectiveness was a between group comparison of the percent reduction in weekly partial seizure frequency relative to placebo over the entire randomized treatment period (titration + evaluation period). Secondary outcome variables included the responder rate (incidence of patients with ≥50% reduction from baseline in partial-onset seizure frequency). The results of the analysis of Period A are displayed in Table 8.

Table 8: Reduction in Mean Over Placebo in Weekly Frequency of Partial-Onset Seizures in Study 2: Period A
 | Placebo (N=111) | Levetiracetam 1000 mg/day (N=106) | Levetiracetam 2000 mg/day (N=105)
Percent reduction in partial seizure frequency over placebo | – | 17.1% [Statistically significant versus placebo] | 21.4%

The percentage of patients (y-axis) who achieved ≥50% reduction in weekly seizure rates from baseline in partial-onset seizure frequency over the entire randomized treatment period (titration + evaluation period) within the three treatment groups (x-axis) is presented in Figure 2.

Figure 2: Responder Rate (≥50% Reduction from Baseline) in Study 2: Period A

The comparison of levetiracetam 2000 mg/day to levetiracetam 1000 mg/day for responder rate was statistically significant (P=0.02). Analysis of the trial as a cross-over yielded similar results.

Study 3

Study 3 was a double-blind, placebo-controlled, parallel-group study conducted at 47 centers in Europe comparing levetiracetam 3000 mg/day (N=180) and placebo (N=104) in patients with refractory partial-onset seizures, with or without secondary generalization, receiving only one concomitant AED. Study drug was given in two divided doses. After a prospective baseline period of 12 weeks, patients were randomized to one of two treatment groups described above. The 16-week treatment period consisted of a 4-week titration period, followed by a 12-week fixed dose evaluation period, during which concomitant AED doses were held constant. The primary measure of effectiveness was a between group comparison of the percent reduction in weekly seizure frequency relative to placebo over the entire randomized treatment period (titration + evaluation period). Secondary outcome variables included the responder rate (incidence of patients with ≥50% reduction from baseline in partial-onset seizure frequency). Table 9 displays the results of the analysis of Study 3.

Table 9: Reduction in Mean Over Placebo in Weekly Frequency of Partial-Onset Seizures in Study 3
 | Placebo (N=104) | Levetiracetam 3000 mg/day (N=180)
Percent reduction in partial seizure frequency over placebo | – | 23.0% [Statistically significant versus placebo]

The percentage of patients (y-axis) who achieved ≥50% reduction in weekly seizure rates from baseline in partial-onset seizure frequency over the entire randomized treatment period (titration + evaluation period) within the two treatment groups (x-axis) is presented in Figure 3.

Figure 3: Responder Rate (≥50% Reduction from Baseline) in Study 3

14.2 Myoclonic Seizures in Patients with Juvenile Myoclonic Epilepsy

The effectiveness of levetiracetam as adjunctive therapy in patients with juvenile myoclonic epilepsy (JME) experiencing myoclonic seizures was established in one multicenter, randomized, double-blind, placebo-controlled study, conducted at 37 sites in 14 countries. Of the 120 patients enrolled, 113 had a diagnosis of confirmed or suspected JME. Eligible patients on a stable dose of 1 antiepileptic drug (AED) experiencing one or more myoclonic seizures per day for at least 8 days during the prospective 8-week baseline period were randomized to either levetiracetam or placebo (levetiracetam N=60, placebo N=60). Patients were titrated over 4 weeks to a target dose of 3000 mg/day and treated at a stable dose of 3000 mg/day over 12 weeks (evaluation period). Study drug was given in 2 divided doses. The primary measure of effectiveness was the proportion of patients with at least 50% reduction in the number of days per week with one or more myoclonic seizures during the treatment period (titration + evaluation periods) as compared to baseline. Table 10 displays the results for the 113 patients with JME in this study. Of 120 patients enrolled, 113 had a diagnosis of confirmed or suspected JME. The results are displayed in Table 10.

Table 10: Responder Rate (≥50% Reduction from Baseline) in Myoclonic Seizure Days Per Week For Patients With JME
 | Placebo (N=59) | Levetiracetam (N=54)
Percentage of responders | 23.7% | 60.4% [Statistically significant versus placebo]

14.3 Primary Generalized Tonic-Clonic Seizures

The effectiveness of levetiracetam as adjunctive therapy in patients with idiopathic generalized epilepsy experiencing primary generalized tonic-clonic (PGTC) seizures was established in one multicenter, randomized, double-blind, placebo-controlled study, conducted at 50 sites in 8 countries. Eligible patients on a stable dose of 1 or 2 antiepileptic drugs (AEDs) experiencing at least 3 PGTC seizures during the 8-week combined baseline period (at least one PGTC seizure during the 4 weeks prior to the prospective baseline period and at least one PGTC seizure during the 4-week prospective baseline period) were randomized to either levetiracetam or placebo. The 8-week combined baseline period is referred to as “baseline” in the remainder of this section. The population included 164 patients (levetiracetam N=80, placebo N=84) with idiopathic generalized epilepsy (predominately juvenile myoclonic epilepsy, juvenile absence epilepsy, childhood absence epilepsy, or epilepsy with Grand Mal seizures on awakening) experiencing primary generalized tonic-clonic seizures. Each of these syndromes of idiopathic generalized epilepsy was well represented in this patient population. Patients were titrated over 4 weeks to a target dose of 3000 mg/day for adults or a pediatric target dose of 60 mg/kg/day and treated at a stable dose of 3000 mg/day (or 60 mg/kg/day for children) over 20 weeks (evaluation period). Study drug was given in 2 equally divided doses per day.

The primary measure of effectiveness was the percent reduction from baseline in weekly PGTC seizure frequency for levetiracetam and placebo treatment groups over the treatment period (titration + evaluation periods). There was a statistically significant decrease from baseline in PGTC frequency in the levetiracetam-treated patients compared to the placebo-treated patients.

Table 11: Median Percent Reduction from Baseline in PGTC Seizure Frequency per Week
 | Placebo (N=84) | Levetiracetam (N=78)
Percentage reduction in PGTC seizure frequency | 44.6% | 77.6% [Statistically significant versus placebo]

The percentage of patients (y-axis) who achieved ≥50% reduction in weekly seizure rates from baseline in PGTC seizure frequency over the entire randomized treatment period (titration + evaluation period) within the two treatment groups (x-axis) is presented in Figure 4.

Figure 4: Responder Rate (≥50% Reduction from Baseline) in PGTC Seizure Frequency per Week

16 HOW SUPPLIED/STORAGE AND HANDLING

16.1 How Supplied

Levetiracetam in Sodium Chloride Injection is a clear, colorless, sterile solution that is available in a single-dose 100 mL dual port bag with an aluminum over wrap. The container closure is not made with natural rubber latex. It is available in the following presentations:

Strength | Package | NDC Number
500 mg/100 mL (5 mg/mL) | 1 single-dose bag | 44567-501-01
500 mg/100 mL (5 mg/mL) | 10 bags per carton | 44567-501-10
1000 mg/100 mL (10 mg/mL) | 1 single-dose bag | 44567-502-01
1000 mg/100 mL (10 mg/mL) | 10 bags per carton | 44567-502-10
1500 mg/100 mL (15 mg/mL) | 1 single-dose bag | 44567-503-01
1500 mg/100 mL (15 mg/mL) | 10 bags per carton | 44567-503-10

16.2 Storage

Store at 20°C to 25°C (68°F to 77°F) [see USP Controlled Room Temperature].

17 PATIENT COUNSELING INFORMATION

Psychiatric Reactions and Changes in Behavior

Advise patients and their caregivers that levetiracetam may cause changes in behavior (e.g., aggression, agitation, anger, anxiety, apathy, depression, hostility, and irritability) and psychotic symptoms [see Warnings and Precautions (5.1)].

Effects on Driving or Operating Machinery

Inform patients that levetiracetam may cause dizziness and somnolence. Inform patients not to drive or operate machinery until they have gained sufficient experience on levetiracetam to gauge whether it adversely affects their ability to drive or operate machinery [see Warnings and Precautions (5.2)].

Anaphylaxis and Angioedema

Advise patients to discontinue levetiracetam and seek medical care if they develop signs and symptoms of anaphylaxis or angioedema [see Warnings and Precautions (5.3)].

Dermatological Adverse Reactions

Advise patients that serious dermatological adverse reactions have occurred in patients treated with levetiracetam and instruct them to call their physician immediately if a rash develops [see Warnings and Precautions (5.4)].

DRESS/Multiorgan Hypersensitivity

Instruct patients and caregivers that a fever or rash associated with signs of other organ system involvement (e.g., lymphadenopathy, hepatic dysfunction) may be drug-related and should be reported to their healthcare provider immediately. Levetiracetam should be discontinued immediately if a serious hypersensitivity reaction is suspected [see Warnings and Precautions (5.5)].

Pregnancy

Advise patients to notify their healthcare provider if they become pregnant or intend to become pregnant during levetiracetam therapy. Encourage patients to enroll in the North American Antiepileptic Drug (NAAED) pregnancy registry if they become pregnant [see Use In Specific Populations (8.1)].

Manufactured for:
WG Critical Care, LLC
Paramus, NJ 07652

Made in Switzerland

Package/Label Display Panel

NDC 44567-501-01

Levetiracetam in 0.82% Sodium Chloride Injection

500 mg/100 mL

(5 mg/mL)

For Intravenous Infusion Only

Package/Label Display Panel

NDC 44567-502-01

Levetiracetam in 0.75% Sodium Chloride Injection

1000 mg/100 mL

(10 mg/mL)

For Intravenous Infusion Only

Package/Label Display Panel

NDC 44567-503-01

Levetiracetam in 0.54% Sodium Chloride Injection

1500 mg/100 mL

(15 mg/mL)

For Intravenous Infusion Only